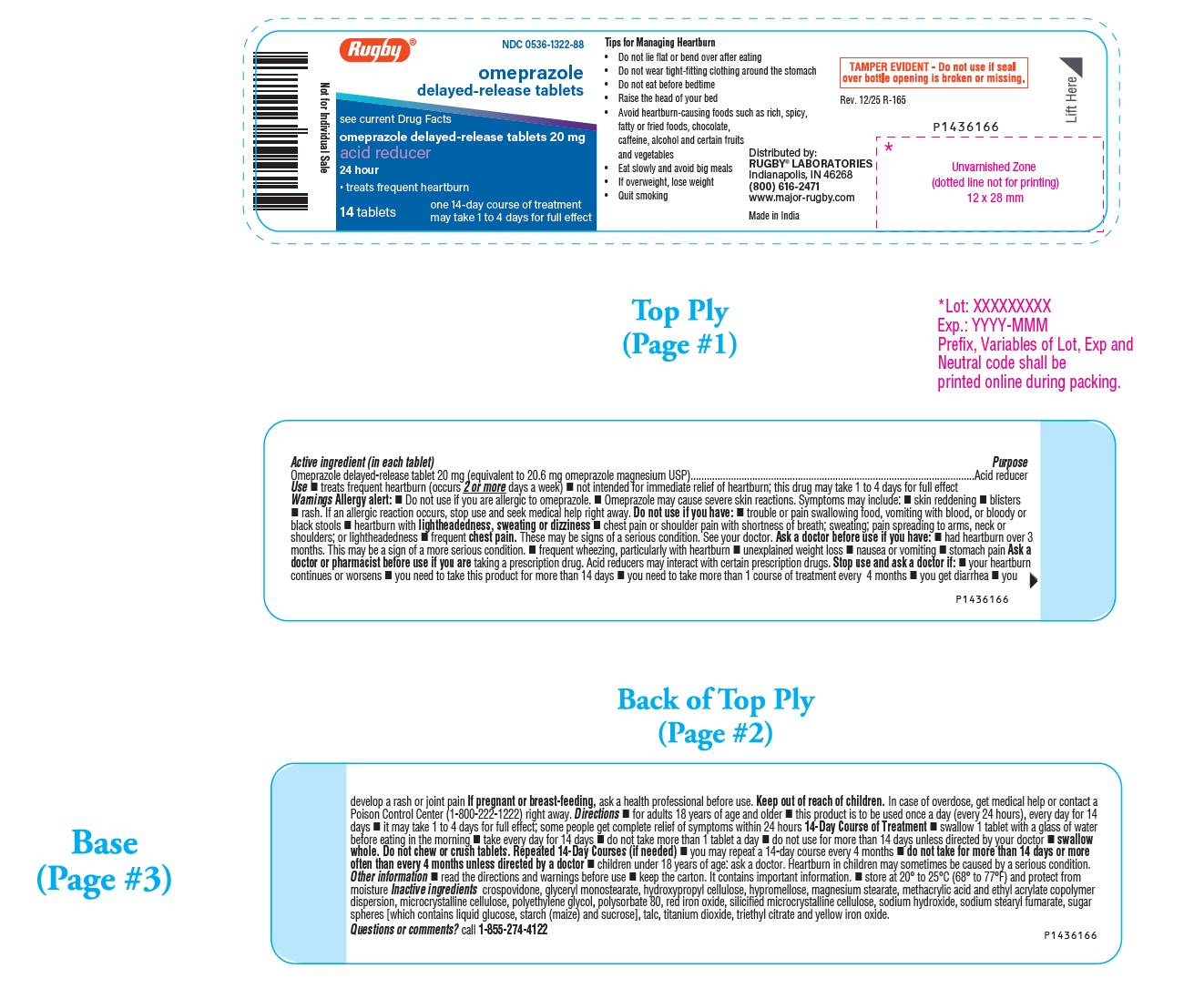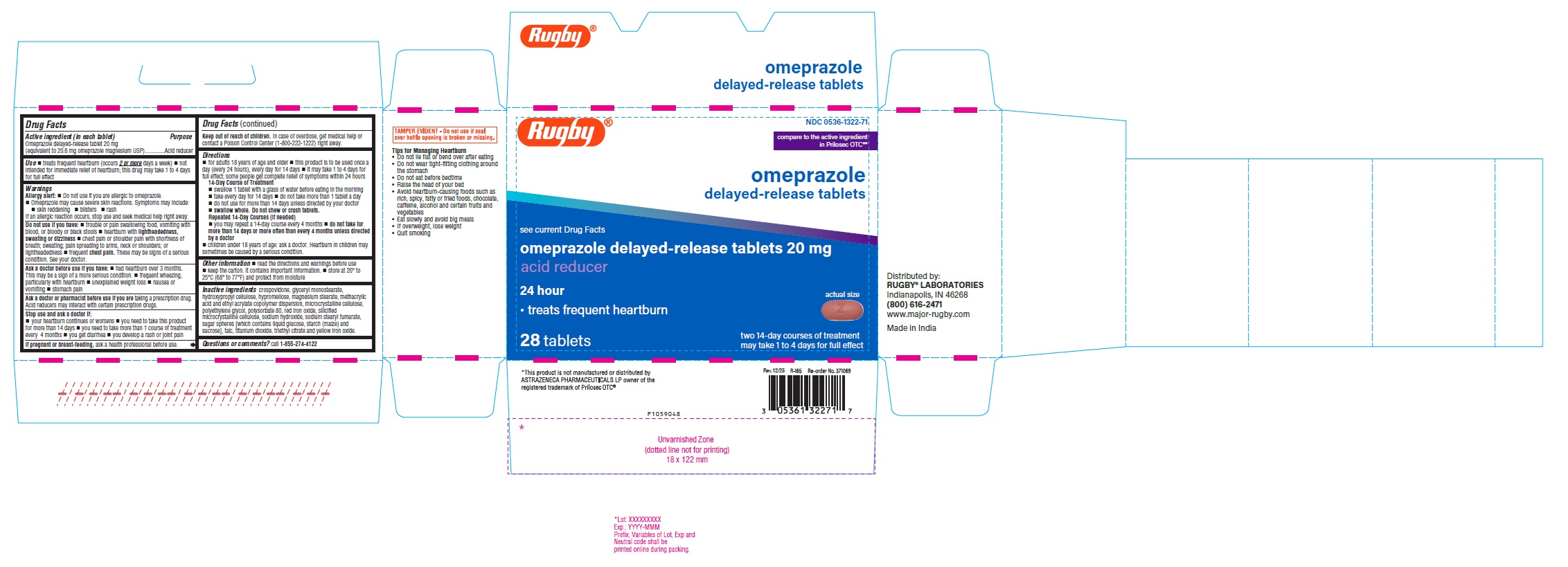 DRUG LABEL: Acid Reducer
NDC: 0536-1322 | Form: TABLET, DELAYED RELEASE
Manufacturer: Rugby Laboratories
Category: otc | Type: Human OTC Drug Label
Date: 20260204

ACTIVE INGREDIENTS: OMEPRAZOLE MAGNESIUM 20 mg/1 1
INACTIVE INGREDIENTS: CROSPOVIDONE (35 .MU.M); GLYCERYL MONOSTEARATE; HYDROXYPROPYL CELLULOSE (90000 WAMW); HYPROMELLOSE 2910 (5 MPA.S); MAGNESIUM STEARATE; METHACRYLIC ACID - ETHYL ACRYLATE COPOLYMER (1:1) TYPE A; MICROCRYSTALLINE CELLULOSE; POLYETHYLENE GLYCOL 4000; POLYSORBATE 80; FERRIC OXIDE RED; SILICON DIOXIDE; SODIUM HYDROXIDE; SODIUM STEARYL FUMARATE; DEXTROSE, UNSPECIFIED FORM; STARCH, CORN; SUCROSE; TALC; TITANIUM DIOXIDE; TRIETHYL CITRATE; FERRIC OXIDE YELLOW; HYDROXYPROPYL CELLULOSE (45000 WAMW); HYPROMELLOSE 2910 (6 MPA.S)

Tips for Managing Heartburn

- Do not lie flat or bend over after eating
- Do not wear tight-fitting clothing around the stomach
- Do not eat before bedtime
- Raise the head of your bed
- Avoid heartburn-causing foods such as rich, spicy, fatty or fried foods, chocolate, caffeine, alcohol and certain fruits and vegetables
- Eat slowly and avoid big meals
- If overweight, lose weight
- Quit smoking

Active ingredient (in each tablet)

Omeprazole delayed-release tablet 20 mg (equivalent to 20.6 mg omeprazole magnesium USP)

Purpose

Acid reducer

Use

- treats frequent heartburn (occurs 2 or more days a week)
- not intended for immediate relief of heartburn; this drug may take 1 to 4 days for full effect

Warnings

Allergy alert:

- Do not use if you are allergic to omeprazole.
- Omeprazole may cause severe skin reactions. Symptoms may include:
  • skin reddening • blisters • rash

If an allergic reaction occurs, stop use and seek medical help right away.

Do not use if you have:

- trouble or pain swallowing food, vomiting with blood, or bloody or black stools
- heartburn with lightheadedness, sweating or dizziness
- chest pain or shoulder pain with shortness of breath; sweating; pain spreading to arms, neck or shoulders; or lightheadedness
- frequent chest pain

These may be signs of a serious condition. See your doctor.

Ask a doctor before use if you have:

- had heartburn over 3 months. This may be a sign of a more serious condition.
- frequent wheezing, particularly with heartburn
- unexplained weight loss
- nausea or vomiting
- stomach pain

Ask a doctor or pharmacist before use if you are taking a prescription drug.

Acid reducers may interact with certain prescription drugs.

Stop use and ask a doctor if:

- your heartburn continues or worsens
- you need to take this product for more than 14 days
- you need to take more than 1 course of treatment every 4 months
- you get diarrhea
- you develop a rash or joint pain

PREGNANCY OR BREAST FEEDING

If pregnant or breast-feeding, ask a health professional before use.

Keep out of reach of children.

In case of overdose, get medical help or contact a Poison Control Center (1-800-222-1222) right away.

Directions

- for adults 18 years of age and older
- this product is to be used once a day (every 24 hours), every day for 14 days
- it may take 1 to 4 days for full effect; some people get complete relief of symptoms within 24 hours

14-Day Course of Treatment

- swallow 1 tablet with a glass of water before eating in the morning
- take every day for 14 days
- do not take more than 1 tablet a day
- do not use for more than 14 days unless directed by your doctor
- swallow whole. Do not chew or crush tablets.

Repeated 14-Day Courses (if needed)

- you may repeat a 14-day course every 4 months
- do not take for more than 14 days or more often than every 4 months unless directed by a doctor
- children under 18 years of age: ask a doctor. Heartburn in children may sometimes be caused by a serious condition.

Other information

- read the directions and warnings before use
- keep the carton. It contains important information.
- store at 20º to 25ºC (68º to 77ºF) and protect from moisture

Inactive ingredients

crospovidone, glyceryl monostearate, hydroxypropyl cellulose, hypromellose, magnesium stearate, methacrylic acid and ethyl acrylate copolymer dispersion, microcrystalline cellulose, polyethylene glycol, polysorbate 80, red iron oxide, silicified microcrystalline cellulose, sodium hydroxide, sodium stearyl fumarate, sugar spheres [which contains liquid glucose, starch (maize) and sucrose], talc, titanium dioxide, triethyl citrate and yellow iron oxide.

Questions or comments?

call 1-855-274-4122
Distributed by:
RUGBY® LABORATORIES
Indianapolis, IN 46268
(800) 616-2471
www.major-rugby.com
Made in India

PACKAGE LABEL-PRINCIPAL DISPLAY PANEL - 20 mg (14 Tablet Bottle)

Rugby® NDC 0536-1322-88
omeprazole
delayed-release tablets
see current Drug Facts
omeprazole delayed-release tablets 20 mg
acid reducer
24 hour

- treats frequent heartburn

14 tablets one 14-day course of treatment
may take 1 to 4 days for full effect

PACKAGE LABEL-PRINCIPAL DISPLAY PANEL - 20 mg Container Carton Label

Rugby® NDC 0536-1322-71
Compare to the active ingredient
in Prilsec OTC®*

omeprazole
delayed-release tablets

see current Drug Facts
omeprazole delayed-release tablets 20 mg
acid reducer

24 hour

- treats frequent heartburn actual size

28 tablets two 14-day courses of treatment
may take 1 to 4 days for full effect